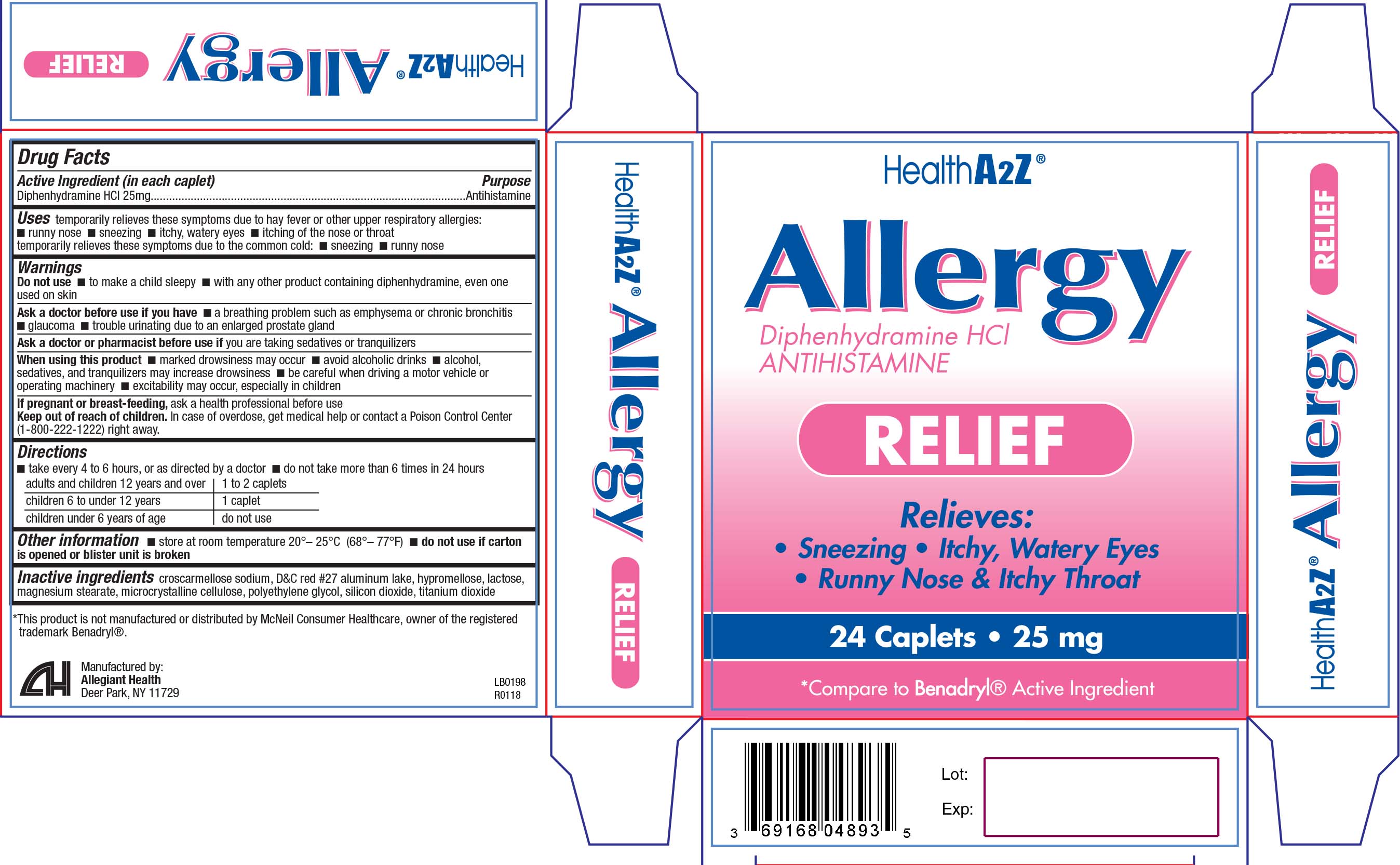 DRUG LABEL: Allergy
NDC: 69168-048 | Form: TABLET
Manufacturer: Allegiant Health
Category: otc | Type: HUMAN OTC DRUG LABEL
Date: 20181107

ACTIVE INGREDIENTS: DIPHENHYDRAMINE HYDROCHLORIDE 25 mg/1 1
INACTIVE INGREDIENTS: CROSCARMELLOSE SODIUM; D&C RED NO. 27; HYPROMELLOSES; LACTOSE, UNSPECIFIED FORM; MAGNESIUM STEARATE; CELLULOSE, MICROCRYSTALLINE; POLYETHYLENE GLYCOL, UNSPECIFIED; SILICON DIOXIDE; TITANIUM DIOXIDE

Drug Facts

Active ingredient

Diphenhydramine HCl 25 mg

Purpose

Antihistamine

Uses

temporarily relieves these symptoms due to hay fever or other upper respiratory allergies:

- runny nose
- sneezing
- itchy, watery eyes
- itching of the nose or throat

temporarily relieves these symptoms due to the common cold:

- sneezing
- runny nose

Warnings

Do not use

- to make a child sleepy
- with any other product containing diphenhydramine, even one used on skin

Ask a doctor if you have

- a breathing problem such as emphysema or chronic bronchitis
- glaucoma
- trouble urinating due to an enlarged prostate gland

Ask a doctor or pharmacist before use if you

are taking sedatives or tranquilizers

When using this product

- marked drowsiness may occur
- avoid alcoholic drinks
- alcohol, sedatives, and tranquilizers may increase drowsiness
- be careful when driving a motor vehicle or operating machinery
- excitability may occur, especially in children

If pregnant or breast-feeding

ask a health professional before use

Keep Out of Reach of Children

In case of overdose, get medical help or contact a Poison Control Center (1-800-222-1222) right away.

Directions

take every 4 to 6 hours, or as directed by a doctor

do not take more than 6 times in 24 hours

adults and children 12 years and over: 1 to 2 caplets

children 6 to under 12 years: 1 caplet

children under 6 years of age: do not use

Inactive Ingredients

croscarmellose sodium, D&C red #27 aluminum lake, hypromellose, lactose, magnesium stearate, microcrystalline cellulose, polyethylene glycol, silicon dioxide, titanium dioxide

Package/Label Principal Display Panel

Diphenhydramine HCl 25mg